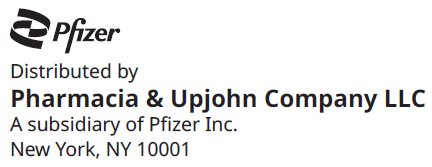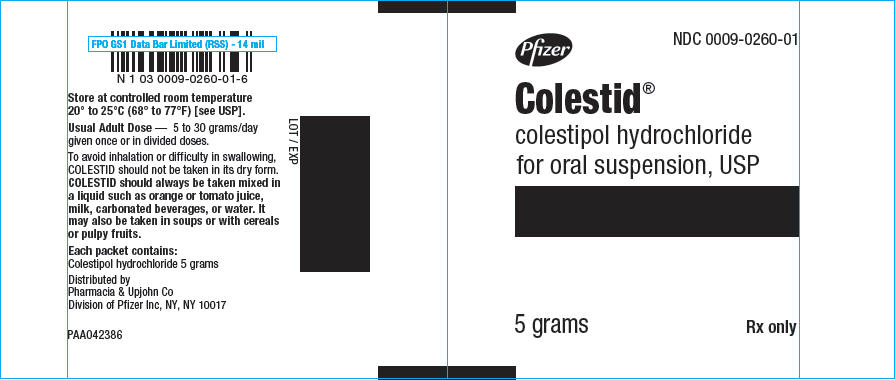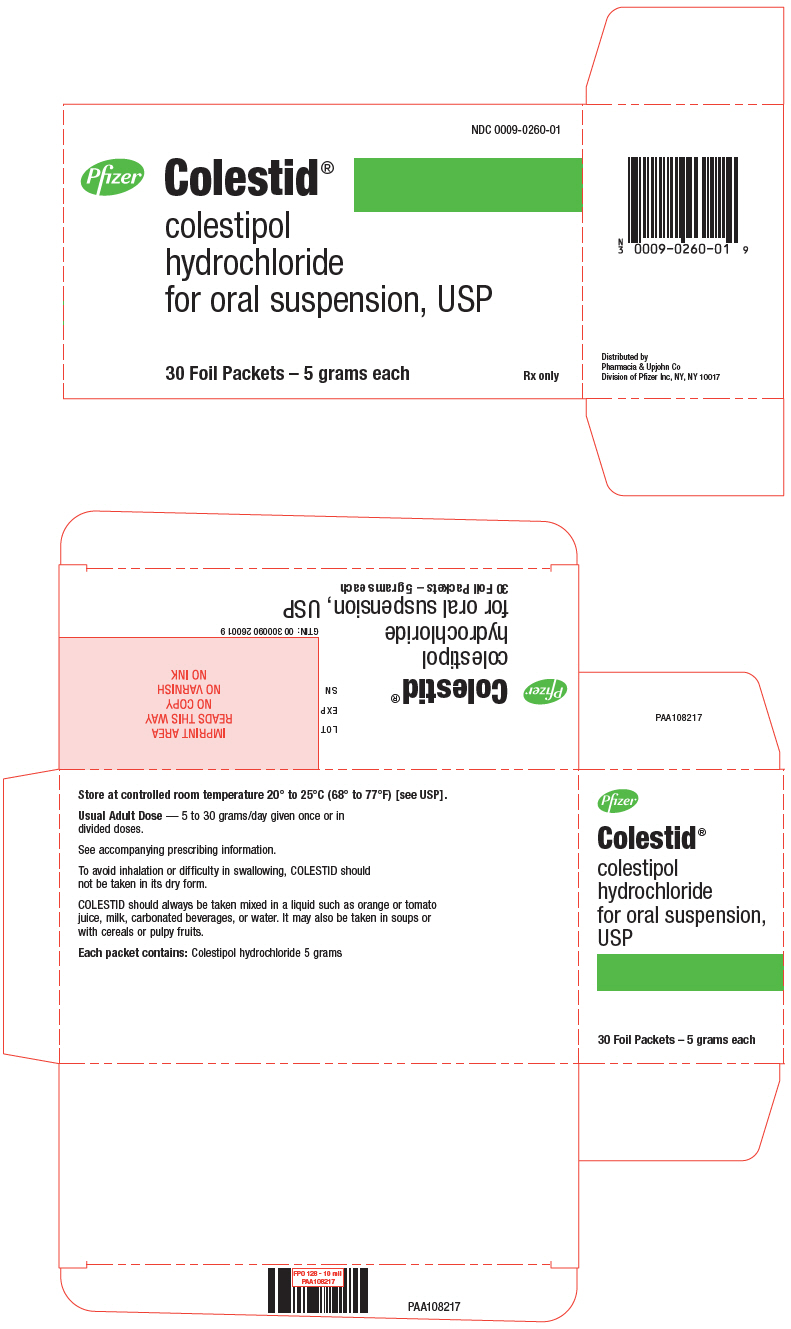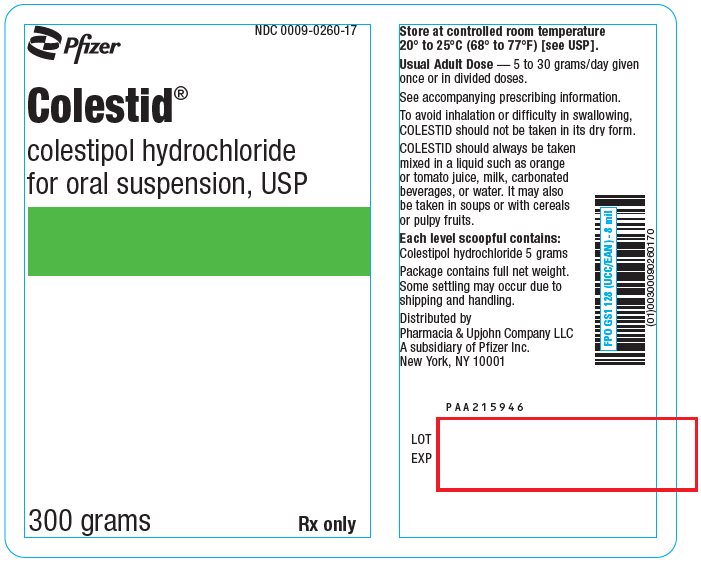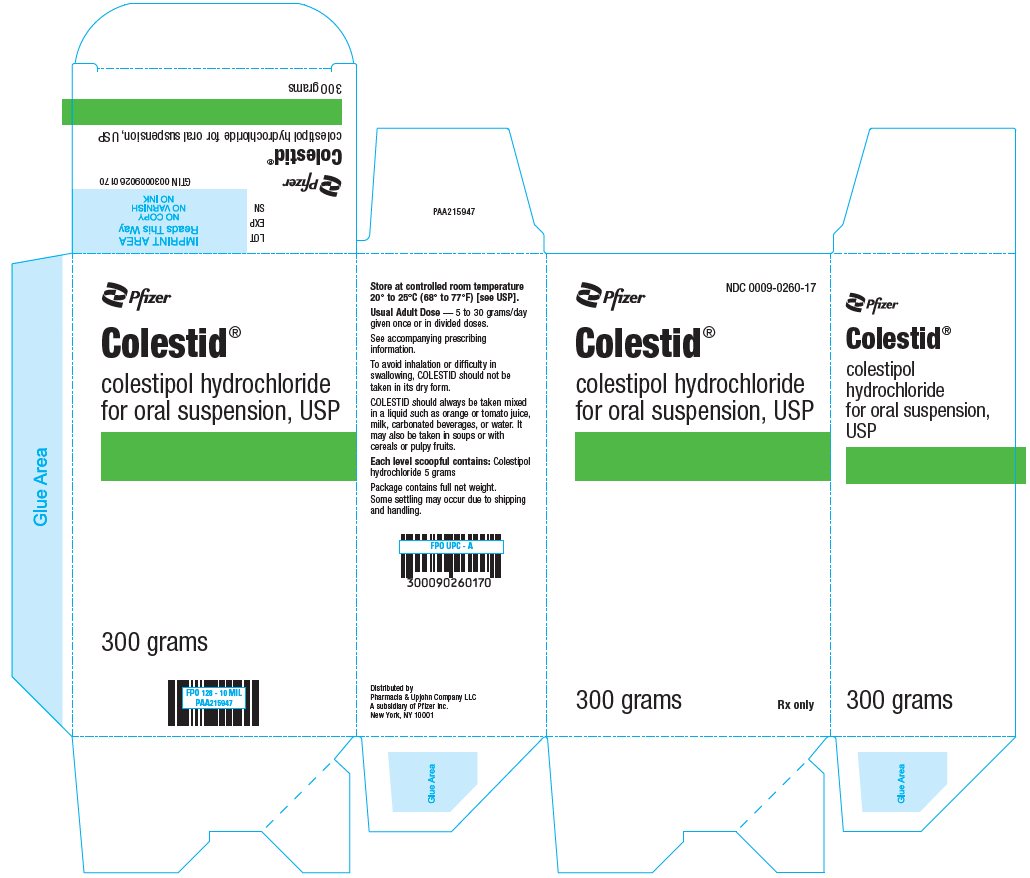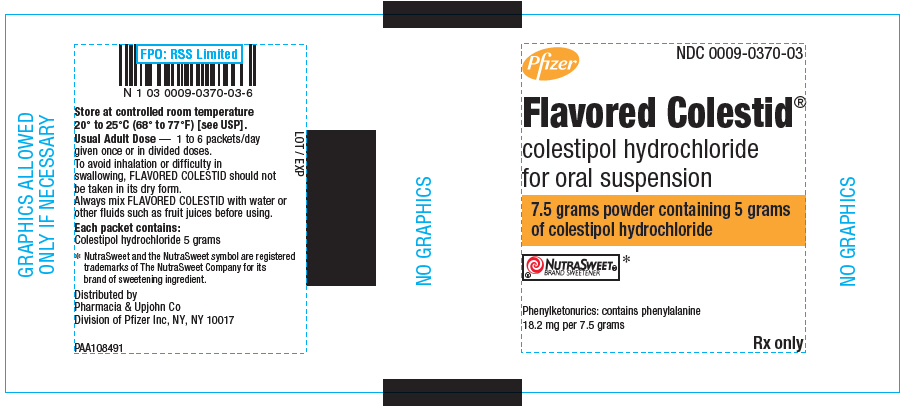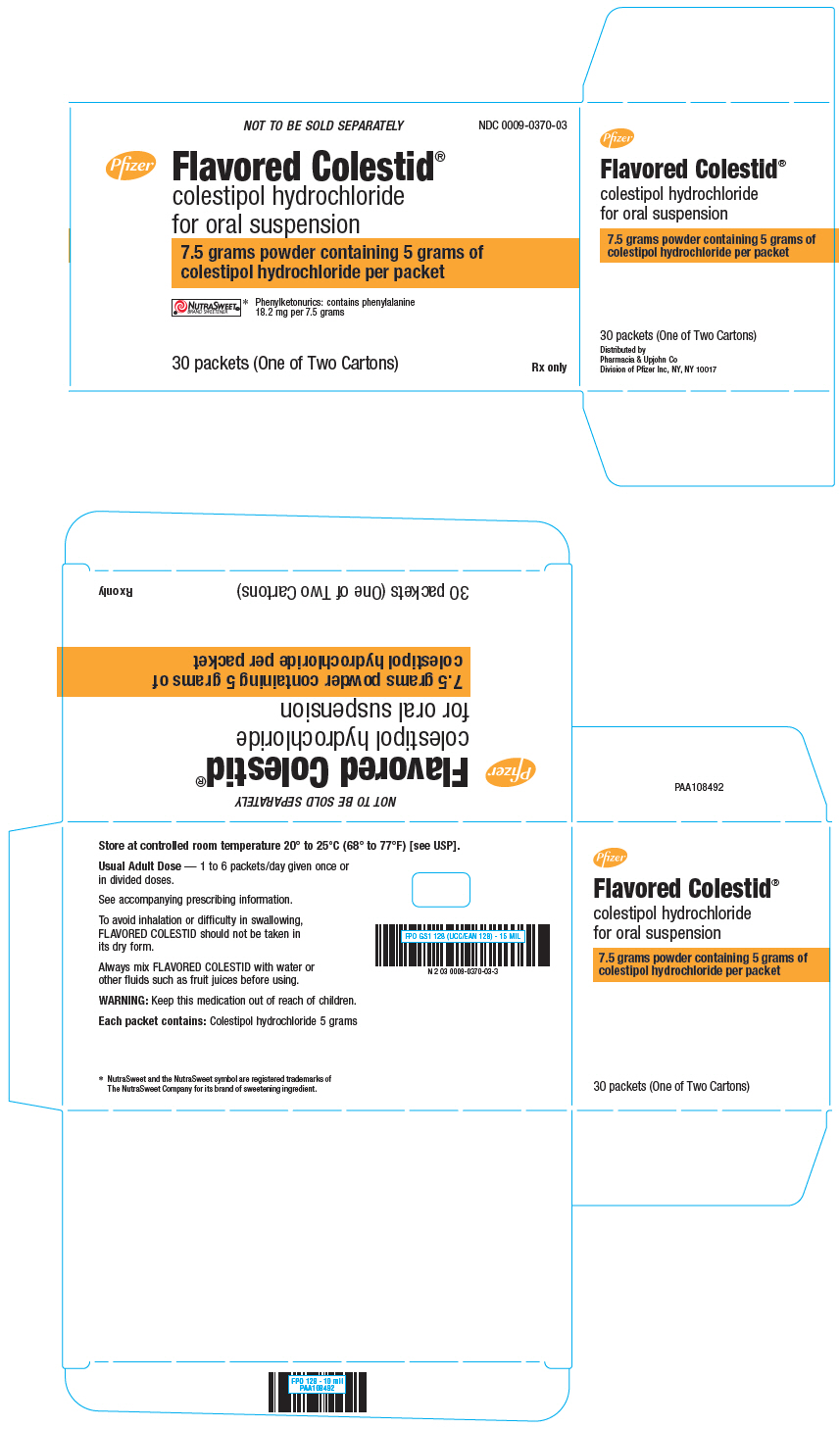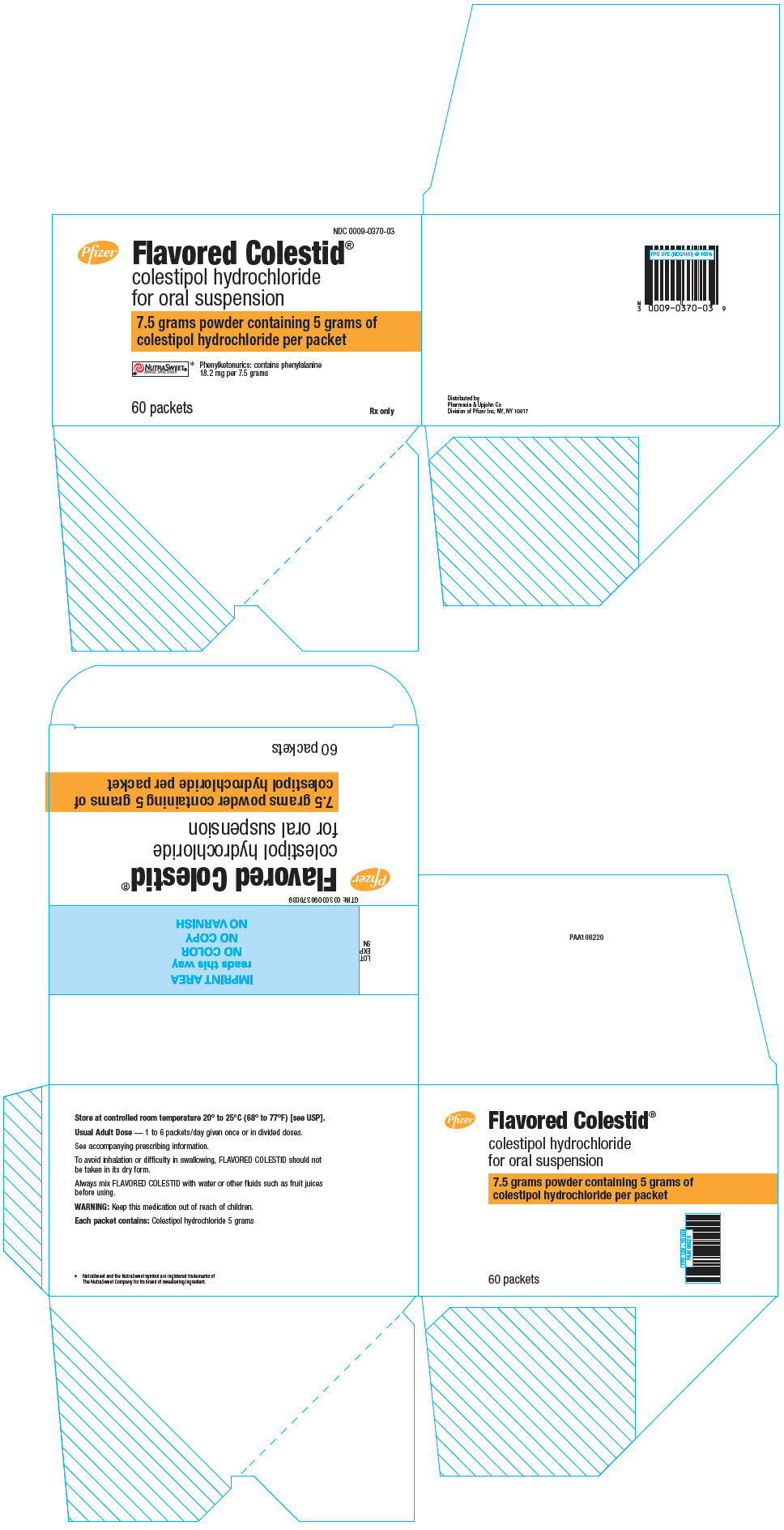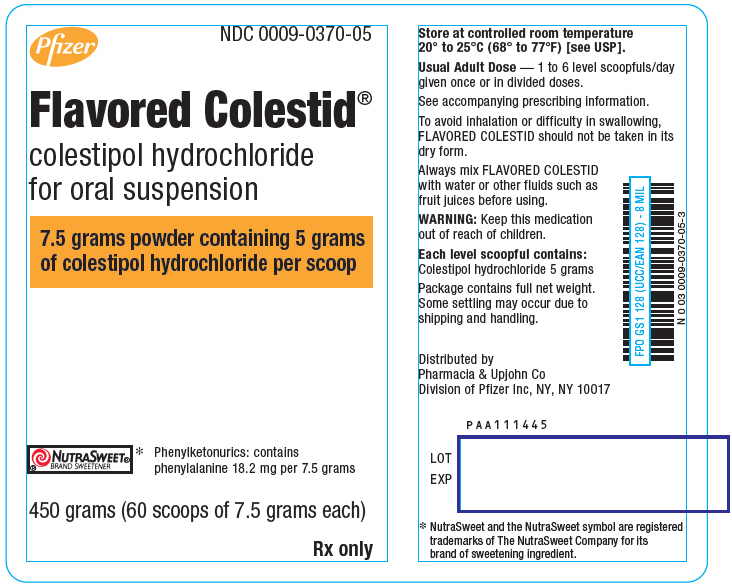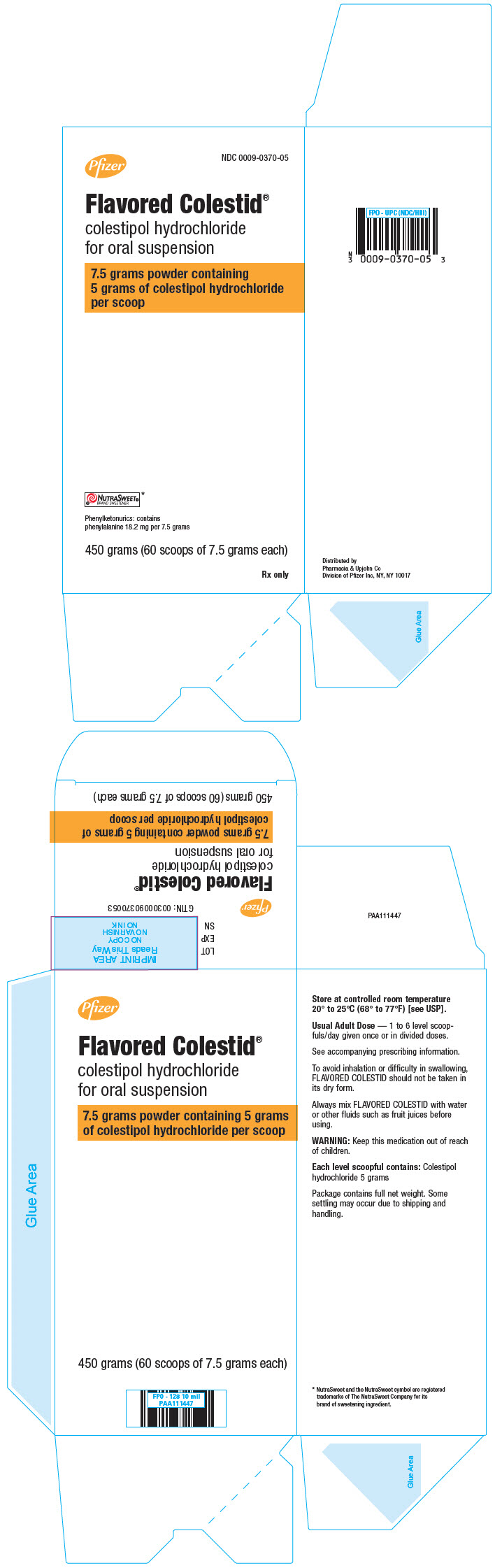 DRUG LABEL: Colestid
NDC: 0009-0260 | Form: GRANULE, FOR SUSPENSION
Manufacturer: Pharmacia & Upjohn Company LLC
Category: prescription | Type: HUMAN PRESCRIPTION DRUG LABEL
Date: 20240627

ACTIVE INGREDIENTS: COLESTIPOL HYDROCHLORIDE 5 g/5 g
INACTIVE INGREDIENTS: SILICON DIOXIDE

Colestid®
Flavored Colestid®
colestipol hydrochloride for oral
suspension

DESCRIPTION

COLESTID Granules and FLAVORED COLESTID Granules contain colestipol hydrochloride, which is a lipid lowering agent for oral use. Colestipol hydrochloride is an insoluble, high molecular weight basic anion-exchange copolymer of diethylenetriamine and 1-chloro-2, 3-epoxypropane, with approximately 1 out of 5 amine nitrogens protonated (chloride form). It is a light yellow water-insoluble resin which is hygroscopic and swells when suspended in water or aqueous fluids.

COLESTID is tasteless and odorless. Inactive ingredient: silicon dioxide. One dose (1 packet or 1 level teaspoon) of COLESTID contains 5 grams of colestipol hydrochloride. FLAVORED COLESTID is orange flavored and light orange in color. One dose (1 packet or 1 level scoopful) of FLAVORED COLESTID is approximately 7.5 grams powder which contains 5 grams of colestipol hydrochloride. This product also contains the following inactive ingredients: aspartame, beta carotene, citric acid, flavor (natural and artificial), glycerine, maltol, mannitol, and methylcellulose.

CLINICAL PHARMACOLOGY

Cholesterol is the major, and probably the sole precursor of bile acids. During normal digestion, bile acids are secreted via the bile from the liver and gall bladder into the intestines. Bile acids emulsify the fat and lipid materials present in food, thus facilitating absorption. A major portion of the bile acids secreted is reabsorbed from the intestines and returned via the portal circulation to the liver, thus completing the enterohepatic cycle. Only very small amounts of bile acids are found in normal serum.

Colestipol hydrochloride binds bile acids in the intestine forming a complex that is excreted in the feces. This nonsystemic action results in a partial removal of the bile acids from the enterohepatic circulation, preventing their reabsorption. Since colestipol hydrochloride is an anion exchange resin, the chloride anions of the resin can be replaced by other anions, usually those with a greater affinity for the resin than chloride ion.

Colestipol hydrochloride is hydrophilic, but it is virtually water insoluble (99.75%) and it is not hydrolyzed by digestive enzymes. The high molecular weight polymer in colestipol hydrochloride apparently is not absorbed. In humans, less than 0.17% of a single ^14C-labeled colestipol hydrochloride dose is excreted in the urine when given following 60 days of chronic dosing of 20 grams of colestipol hydrochloride per day.

The increased fecal loss of bile acids due to colestipol hydrochloride administration leads to an increased oxidation of cholesterol to bile acids. This results in an increase in the number of low-density lipoprotein (LDL) receptors, increased hepatic uptake of LDL and a decrease in beta lipoprotein or low density lipoprotein serum levels, and a decrease in serum cholesterol levels. Although colestipol hydrochloride produces an increase in the hepatic synthesis of cholesterol in man, serum cholesterol levels fall.

There is evidence to show that this fall in cholesterol is secondary to an increased rate of clearance of cholesterol-rich lipoproteins (beta or low density lipoproteins) from the plasma. Serum triglyceride levels may increase or remain unchanged in colestipol hydrochloride treated patients.

The decline in serum cholesterol levels with colestipol hydrochloride treatment is usually evident by one month. When colestipol hydrochloride is discontinued, serum cholesterol levels usually return to baseline levels within one month. Periodic determinations of serum cholesterol levels as outlined in the National Cholesterol Education Program (NCEP) guidelines should be done to confirm a favorable initial and long-term response^1.

In a large, placebo-controlled, multiclinic study, the LRC-CPPT,^2 hypercholesterolemic subjects treated with cholestyramine, a bile-acid sequestrant with a mechanism of action and an effect on serum cholesterol similar to that of colestipol hydrochloride, had reductions in total and low-density lipoprotein cholesterol (LDL-C). Over the seven-year study period the cholestyramine group experienced a 19% reduction (relative to the incidence in the placebo group) in the combined rate of coronary heart disease death plus non-fatal myocardial infarction (cumulative incidences of 7% cholestyramine and 8.6%, placebo). The subjects included in the study were middle-aged men (age 35–59) with serum cholesterol-levels above 265 mg/dL, LDL-C above 175 mg/dL on a moderate cholesterol-lowering diet, and no history of heart disease. It is not clear to what extent these findings can be extrapolated to other segments of the hypercholesterolemic population not studied.

Treatment with colestipol hydrochloride results in a significant increase in lipoprotein LpAI. Lipoprotein LpAI is one of the two major lipoprotein particles within the high-density lipoprotein (HDL) density range^3, and has been shown in cell culture to promote cholesterol efflux or removal from cells^4. Although the significance of this finding has not been established in clinical studies, the elevation of the lipoprotein LpAI particle within the HDL fraction is consistent with an antiatherogenic effect of colestipol hydrochloride, even though little change is observed in HDL cholesterol.

In patients with heterozygous familial hypercholesterolemia who have not obtained an optimal response to colestipol hydrochloride alone in maximal doses, the combination of colestipol hydrochloride and nicotinic acid has been shown to further lower serum cholesterol, triglyceride, and LDL cholesterol (LDL-C) values. Simultaneously, HDL cholesterol (HDL-C) values increased significantly. In many such patients it is possible to normalize serum lipid values.^5–7

Preliminary evidence suggests that the cholesterol-lowering effects of lovastatin and the bile acid sequestrant, colestipol hydrochloride, are additive.

The effect of intensive lipid-lowering therapy on coronary atherosclerosis has been assessed by arteriography in hyperlipidemic patients. In these randomized, controlled clinical trials, patients were treated for two to four years by either conventional measures (diet, placebo, or in some cases low-dose resin), or with intensive combination therapy using diet and COLESTID Granules plus either nicotinic acid or lovastatin. When compared to conventional measures, intensive lipid-lowering combination therapy significantly reduced the frequency of progression and increased the frequency of regression of coronary atherosclerotic lesions in patients with or at risk for coronary artery disease.^8–11

INDICATIONS AND USAGE

Since no drug is innocuous, strict attention should be paid to the indications and contraindications, particularly when selecting drugs for chronic long-term use.

COLESTID Granules and FLAVORED COLESTID Granules are indicated as adjunctive therapy to diet for the reduction of elevated serum total and low-density lipoprotein (LDL) cholesterol in patients with primary hypercholesterolemia (elevated low density lipoproteins [LDL] cholesterol) who do not respond adequately to diet. Generally, COLESTID and FLAVORED COLESTID have no clinically significant effect on serum triglycerides, but with its use triglyceride levels may be raised in some patients.

Therapy with lipid-altering agents should be a component of multiple risk factor intervention in those individuals at significantly increased risk for atherosclerotic vascular disease due to hypercholesterolemia. Treatment should begin and continue with dietary therapy (see NCEP guidelines). A minimum of six months of intensive dietary therapy and counseling should be carried out prior to initiation of drug therapy. Shorter periods may be considered in patients with severe elevations of LDL-C or with definite CHD.

According to the NCEP guidelines, the goal of treatment is to lower LDL-C, and LDL-C is to be used to initiate and assess treatment response. Only if LDL-C levels are not available, should the Total-C be used to monitor therapy. The NCEP treatment guidelines are shown below.

 |  | LDL-Cholesterol mg/dL (mmol/L)
Definite Atherosclerotic Disease [Coronary heart disease or peripheral vascular disease (including symptomatic carotid artery disease).] | Two or More Other Risk Factors [Other risk factors for coronary heart disease (CHD) include: age (males: ≥45 years; females: ≥55 years or premature menopause without estrogen replacement therapy); family history of premature CHD; current cigarette smoking; hypertension; confirmed HDL-C <35 mg/dL (0.91 mmol/L); and diabetes mellitus. Subtract one risk factor if HDL-C is ≥60 mg/dL (1.6 mmol/L).] | Initiation Level | Goal
No | No | ≥190 (≥4.9) | <160 (<4.1)
No | Yes | ≥160 (≥4.1) | <130 (<3.4)
Yes | Yes or No | ≥130 (≥3.4) | ≤100 (≤2.6)

CONTRAINDICATIONS

COLESTID Granules and FLAVORED COLESTID Granules are contraindicated in those individuals who have shown hypersensitivity to any of its components.

WARNINGS

TO AVOID ACCIDENTAL INHALATION OR ESOPHAGEAL DISTRESS, COLESTID GRANULES AND FLAVORED COLESTID GRANULES SHOULD NOT BE TAKEN IN ITS DRY FORM. ALWAYS MIX COLESTID AND FLAVORED COLESTID WITH WATER OR OTHER FLUIDS BEFORE INGESTING.

PHENYLKETONURICS: FLAVORED COLESTID CONTAINS 18.2 MG PHENYLALANINE PER 7.5-GRAM DOSE.

PRECAUTIONS

Prior to initiating therapy with COLESTID Granules and FLAVORED COLESTID Granules, secondary causes of hypercholesterolemia (e.g., poorly controlled diabetes mellitus, hypothyroidism, nephrotic syndrome, dysproteinemias, obstructive liver disease, other drug therapy, alcoholism), should be excluded, and a lipid profile performed to assess Total cholesterol, HDL-C, and triglycerides (TG). For individuals with TG less than 400 mg/dL (<4.5 mmol/L), LDL-C can be estimated using the following equation:

LDL-C = Total cholesterol - [ (Triglycerides / 5)+HDL-C]

For TG levels >400 mg/dL, this equation is less accurate and LDL-C concentrations should be determined by ultracentrifugation. In hypertriglyceridemic patients, LDL-C may be low or normal despite elevated Total-C. In such cases COLESTID and FLAVORED COLESTID may not be indicated.

Because it sequesters bile acids, colestipol hydrochloride may interfere with normal fat absorption and thus may reduce absorption of folic acid and fat soluble vitamins such as A, D, and K.

Chronic use of colestipol hydrochloride may be associated with an increased bleeding tendency due to hypoprothrombinemia from vitamin K deficiency. This will usually respond promptly to parenteral vitamin K1 and recurrences can be prevented by oral administration of vitamin K1.

Serum cholesterol and triglyceride levels should be determined periodically based on NCEP guidelines to confirm a favorable initial and adequate long-term response.

COLESTID and FLAVORED COLESTID may produce or severely worsen pre-existing constipation. The dosage should be increased gradually in patients to minimize the risk of developing fecal impaction. In patients with pre-existing constipation, the starting dose should be 1 packet or 1 scoop once daily for 5–7 days, increasing to twice daily with monitoring of constipation and of serum lipoproteins, at least twice, 4–6 weeks apart. Increased fluid and fiber intake should be encouraged to alleviate constipation and a stool softener may occasionally be indicated. If the initial dose is well tolerated, the dose may be increased as needed by one dose/day (at monthly intervals) with periodic monitoring of serum lipoproteins. If constipation worsens or the desired therapeutic response is not achieved at one to six doses/day, combination therapy or alternate therapy should be considered. Particular effort should be made to avoid constipation in patients with symptomatic coronary artery disease. Constipation associated with COLESTID and FLAVORED COLESTID may aggravate hemorrhoids.

While there have been no reports of hypothyroidism induced in individuals with normal thyroid function, the theoretical possibility exists, particularly in patients with limited thyroid reserve.

Since colestipol hydrochloride is a chloride form of an anion exchange resin, there is a possibility that prolonged use may lead to the development of hyperchloremic acidosis.

Carcinogenesis, mutagenesis and impairment of fertility

In studies conducted in rats in which cholestyramine resin (a bile acid sequestering agent similar to colestipol hydrochloride) was used as a tool to investigate the role of various intestinal factors, such as fat, bile salts and microbial flora, in the development of intestinal tumors induced by potent carcinogens, the incidence of such tumors was observed to be greater in cholestyramine resin treated rats than in control rats.

The relevance of this laboratory observation from studies in rats with cholestyramine resin to the clinical use of colestipol hydrochloride is not known. In the LRC-CPPT study referred to above, the total incidence of fatal and non-fatal neoplasms was similar in both treatment groups. When the many different categories of tumors are examined, various alimentary system cancers were somewhat more prevalent in the cholestyramine group. The small numbers and the multiple categories prevent conclusions from being drawn. Further follow-up of the LRC-CPPT participants by the sponsors of that study is planned for cause-specific mortality and cancer morbidity.

When colestipol hydrochloride was administered in the diet to rats for 18 months, there was no evidence of any drug related intestinal tumor formation. In the Ames assay, colestipol hydrochloride was not mutagenic.

Use in Pregnancy

Since colestipol hydrochloride is essentially not absorbed systemically (less than 0.17% of the dose), it is not expected to cause fetal harm when administered during pregnancy in recommended dosages. There are no adequate and well controlled studies in pregnant women, and the known interference with absorption of fat soluble vitamins may be detrimental even in the presence of supplementation. The use of COLESTID or FLAVORED COLESTID in pregnancy or by women of childbearing potential requires that the potential benefits of drug therapy be weighed against possible hazards to the mother or child.

Nursing Mother

Caution should be exercised when COLESTID or FLAVORED COLESTID is administered to a nursing mother. The possible lack of proper vitamin absorption described in the "pregnancy" section may have an effect on nursing infants.

Pediatric Use

Safety and effectiveness in the pediatric population have not been established.

Drug Interactions

Since colestipol hydrochloride is an anion exchange resin, it may have a strong affinity for anions other than the bile acids. In vitro studies have indicated that colestipol hydrochloride binds a number of drugs. Therefore, COLESTID and FLAVORED COLESTID resin may delay or reduce the absorption of concomitant oral medication. The interval between the administration of COLESTID and FLAVORED COLESTID and any other medication should be as long as possible. Patients should take other drugs at least one hour before or four hours after COLESTID and FLAVORED COLESTID to avoid impeding their absorption.

Repeated doses of colestipol hydrochloride given prior to a single dose of propranolol in human trials have been reported to decrease propranolol absorption. However, in a follow-up study in normal subjects, single dose administration of colestipol hydrochloride and propranolol and twice-a-day administration for 5 days of both agents did not effect the extent of propranolol absorption, but had a small yet statistically significant effect on its rate of absorption; the time to reach maximum concentration was delayed 30 minutes. Effects on the absorption of other beta-blockers have not been determined. Therefore, patients on propranolol should be observed when COLESTID or FLAVORED COLESTID is either added or deleted from a therapeutic regimen.

Studies in humans show that the absorption of chlorothiazide as reflected in urinary excretion is markedly decreased even when administered one hour before colestipol hydrochloride. The absorption of tetracycline, furosemide, penicillin G, hydrochlorothiazide, and gemfibrozil was significantly decreased when given simultaneously with colestipol hydrochloride; these drugs were not tested to determine the effect of administration one hour before colestipol hydrochloride.

No depressant effect on blood levels in humans was noted when colestipol hydrochloride was administered with any of the following drugs: aspirin, clindamycin, clofibrate, methyldopa, nicotinic acid (niacin), tolbutamide, phenytoin or warfarin. Particular caution should be observed with digitalis preparations since there are conflicting results for the effect of colestipol hydrochloride on the availability of digoxin and digitoxin. The potential for binding of these drugs if given concomitantly is present. Discontinuing colestipol hydrochloride could pose a hazard to health if a potentially toxic drug that is significantly bound to the resin has been titrated to a maintenance level while the patient was taking colestipol hydrochloride.

Bile acid binding resins may also interfere with the absorption of oral phosphate supplements and hydrocortisone.

A study has shown that cholestyramine binds bile acids and reduces mycophenolic acid exposure. As colestipol also binds bile acids, colestipol may reduce mycophenolic acid exposure and potentially reduce efficacy of mycophenolate mofetil.

ADVERSE REACTIONS

Gastrointestinal

The most common adverse reactions are confined to the gastrointestinal tract. To achieve minimal GI disturbance with an optimal LDL-cholesterol lowering effect, a gradual increase of dosage starting with one dose/day is recommended. Constipation is the major single complaint and at times is severe. Most instances of constipation are mild, transient, and controlled with standard treatment. Increased fluid intake and inclusion of additional dietary fiber should be the first step; a stool softener may be added if needed. Some patients require decreased dosage or discontinuation of therapy. Hemorrhoids may be aggravated.

Other, less frequent gastrointestinal complaints consist of abdominal discomfort (abdominal pain and cramping), intestinal gas, (bloating and flatulence), indigestion and heartburn, diarrhea and loose stools, and nausea and vomiting. Bleeding hemorrhoids and blood in the stool have been infrequently reported. Peptic ulceration, cholecystitis, and cholelithiasis have been rarely reported in patients receiving colestipol hydrochloride granules, and are not necessarily drug related.

Transient and modest elevations of aspartate aminotransferase (AST, SGOT), alanine aminotransferase (ALT, SGPT) and alkaline phosphatase were observed on one or more occasions in various patients treated with colestipol hydrochloride.

The following non-gastrointestinal adverse reactions have been reported with generally equal frequency in patients receiving COLESTID Granules, FLAVORED COLESTID Granules, or placebo in clinical studies:

Cardiovascular

Chest pain, angina, and tachycardia have been infrequently reported.

Hypersensitivity

Rash has been infrequently reported. Urticaria and dermatitis have been rarely noted in patients receiving colestipol hydrochloride granules.

Musculoskeletal

Musculoskeletal pain, aches and pains in the extremities, joint pains, arthritis, and backache have been reported.

Neurologic

Headache, migraine headache and sinus headache have been reported. Other infrequently reported complaints include dizziness, light-headedness, and insomnia.

Miscellaneous

Anorexia, fatigue, weakness, shortness of breath, and swelling of the hands or feet, have been infrequently reported.

OVERDOSAGE

Overdosage of COLESTID Granules or FLAVORED COLESTID Granules has not been reported. Should overdosage occur, however, the chief potential harm would be obstruction of the gastrointestinal tract. The location of such potential obstruction, the degree of obstruction and the presence or absence of normal gut motility would determine treatment.

DOSAGE AND ADMINISTRATION

One dose (1 packet or 1 level teaspoon) of COLESTID Granules contains 5 grams of colestipol hydrochloride. One dose (1 packet or 1 level scoopful) of FLAVORED COLESTID Granules is approximately 7.5 grams powder which contains 5 grams of colestipol hydrochloride. The recommended daily adult dose is one to six packets or level scoopfuls given once or in divided doses. Treatment should be started with one dose once or twice daily with an increment of one dose/day at one- or two-month intervals. Appropriate use of lipid profiles as per NCEP guidelines including LDL-cholesterol and triglycerides is advised so that optimal, but not excessive doses are used to obtain the desired therapeutic effect on LDL-cholesterol level. If the desired therapeutic effect is not obtained at one to six doses/day with good compliance and acceptable side effects, combined therapy or alternate treatment should be considered.

To avoid accidental inhalation or esophageal distress, COLESTID and FLAVORED COLESTID should not be taken in its dry form. COLESTID and FLAVORED COLESTID should always be mixed with water or other fluids before ingesting. Patients should take other drugs at least one hour before or four hours after COLESTID or FLAVORED COLESTID to minimize possible interference with their absorption. (See PRECAUTIONS, Drug Interactions.)

Before COLESTID or FLAVORED COLESTID Administration

1. Define the type of hyperlipoproteinemia, as described in NCEP guidelines.
2. Institute a trial of diet and weight reduction.
3. Establish baseline serum total and LDL-cholesterol and triglyceride levels.

During COLESTID or FLAVORED COLESTID Administration

1. The patient should be carefully monitored clinically, including serum cholesterol and triglyceride levels. Periodic determinations of serum cholesterol levels as outlined in the NCEP guidelines should be done to confirm a favorable initial and longer-term response.
2. Failure of total or LDL-cholesterol to fall within the desired range should lead one to first examine dietary and drug compliance. If these are deemed acceptable, combined therapy or alternate treatment should be considered.
3. Significant rise in triglyceride level should be considered as indication for dose reduction, drug discontinuation, or combined or alternate therapy.

Mixing and Administration Guide

COLESTID and FLAVORED COLESTID should always be mixed in a liquid such as water or the beverage of your choice. It may also be taken in soups or with cereals or pulpy fruits. COLESTID or FLAVORED COLESTID should never be taken in its dry form.

FLAVORED COLESTID is an orange-flavored product. Although it may be mixed with a variety of liquids or foods, the selection should be based on patient preference.

With Beverages

1. Add the prescribed amount of COLESTID or FLAVORED COLESTID to a glassful (three ounces or more) of water or the beverage of your choice. A heavy or pulpy juice may minimize complaints relative to consistency.
2. Stir the mixture until the medication is completely mixed. (COLESTID and FLAVORED COLESTID will not dissolve in the liquid.) COLESTID and FLAVORED COLESTID may also be mixed with carbonated beverages, slowly stirred in a large glass; however, this mixture may be associated with GI complaints.

Rinse the glass with a small amount of additional beverage to make sure all the medication is taken.

With cereals, soups, and fruits

COLESTID and FLAVORED COLESTID may be taken mixed with milk in hot or regular breakfast cereals, or even mixed in soups that have a high fluid content. It may also be added to fruits that are pulpy such as crushed pineapple, pears, peaches, or fruit cocktail.

HOW SUPPLIED

COLESTID Granules are available as follows:

Cartons of 30 foil packets — NDC 0009-0260-01
Cartons of 90 foil packets — NDC 0009-0260-04
Bottles of 300 grams with scoop — NDC 0009-0260-17
Bottles of 500 grams with scoop — NDC 0009-0260-02
Each packet or level scoop supplies 5 grams of COLESTID.

FLAVORED COLESTID Granules are available as follows:

Cartons of 60 foil packets — NDC 0009-0370-03
Bottles of 450 grams (equivalent to approximately 60 doses) with scoop — NDC 0009-0370-05
Each packet or each level scoopful supplies approximately 7.5 grams of FLAVORED COLESTID powder containing 5 grams of colestipol hydrochloride.

Store at controlled room temperature 20° to 25° C (68° to 77° F) [see USP].

REFERENCES

1. Summary of the Second Report of the National Cholesterol Education Program (NCEP) Expert Panel on Detection, Evaluation, and Treatment of High Blood Cholesterol in Adults (Adult Treatment Panel II). JAMA 269(23):3015–3023, 1993.
2. Lipid Metabolism-Atherogenesis Branch, National Heart, Lung, and Blood Institute, Bethesda, MD: The Lipid Research Clinics Coronary Primary Prevention Trial Results. I. Reduction in Incidence of Coronary Heart Disease. JAMA 251:351–364, 1984.
3. Parra HJ, et al. Differential electroimmunoassay of human LpA-I lipoprotein particles on ready-to-use plates. Clin. Chem. 36(8):1431–1435, 1990.
4. Barbaras R, et al. Cholesterol efflux from cultured adipose cells is mediated by LpAI particles but not by LpAI:AII particles. Biochem. Biophys. Res. Comm. 142(1):63–69, 1987.
5. Kane JP, et al. Normalization of low-density-lipoprotein levels in heterozygous familial hypercholesterolemia with a combined drug regimen. N Engl. J. Med. 304:251–258, 1981.
6. Illingworth DR, et al. Colestipol plus nicotinic acid in treatment of heterozygous familial hypercholesterolemia. Lancet 1:296–298, 1981.
7. Kuo PT, et al. Familial type II hyperlipoproteinemia with coronary heart disease: Effect of diet-colestipol-nicotinic acid treatment. Chest 79:286–291, 1981.
8. Blankenhorn DH, et al. Beneficial Effects of Combined Colestipol-Niacin Therapy on Coronary Atherosclerosis and Coronary Venous Bypass Grafts. JAMA 257(23):3233–3240, 1987.
9. Cashin-Hemphill L, et al. Beneficial Effects of Colestipol-Niacin on Coronary Atherosclerosis: A 4-Year Follow-up. JAMA 264:3013–3017, 1990.
10. Brown G, et al. Regression of Coronary Artery Disease as a Result of Intensive Lipid-Lowering Therapy in Men with High Levels of Apolipoprotein B. N Engl, J. Med 323:1289–1298, 1990.
11. Kane JP, et al. Regression of Coronary Atherosclerosis During Treatment of Familial Hypercholesterolemia with Combined Drug Regimens. JAMA 264:3007–3012, 1990.

Rx only

LAB-0054-5.0
Revised August 2023

PRINCIPAL DISPLAY PANEL - 5 gram Packet Label

Pfizer
NDC 0009-0260-01

Colestid®
colestipol hydrochloride
for oral suspension, USP

5 grams
Rx only

PRINCIPAL DISPLAY PANEL - 5 gram Packet Carton

NDC 0009-0260-01

Pfizer
Colestid®
colestipol
hydrochloride
for oral suspension, USP

30 Foil Packets – 5 grams each
Rx only

PRINCIPAL DISPLAY PANEL - 300 gram Bottle Label

Pfizer
NDC 0009-0260-17

Colestid®

colestipol hydrochloride
for oral suspension, USP

300 grams
Rx only

PRINCIPAL DISPLAY PANEL - 300 gram Bottle Carton

Pfizer
NDC 0009-0260-17

Colestid®

colestipol hydrochloride
for oral suspension, USP

300 grams
Rx only

PRINCIPAL DISPLAY PANEL - 7.5 gram Packet Label

Pfizer
NDC 0009-0370-03

Flavored Colestid®
colestipol hydrochloride
for oral suspension

7.5 grams powder containing 5 grams
of colestipol hydrochloride

NUTRASWEET®
BRAND SWEETENER*

Phenylketonurics: contains phenylalanine
18.2 mg per 7.5 grams

Rx only

PRINCIPAL DISPLAY PANEL - 30-7.5 gram Packet Carton

NOT TO BE SOLD SEPARATELY
NDC 0009-0370-03

Pfizer
Flavored Colestid®
colestipol hydrochloride
for oral suspension

7.5 grams powder containing 5 grams of
colestipol hydrochloride per packet

NUTRASWEET®
BRAND SWEETENER*

Phenylketonurics: contains phenylalanine
18.2 mg per 7.5 grams

30 packets (One of Two Cartons)
Rx only

PRINCIPAL DISPLAY PANEL - 60-7.5 gram Packet Carton

NDC 0009-0370-03

Pfizer
Flavored Colestid®
colestipol hydrochloride
for oral suspension

7.5 grams powder containing 5 grams of
colestipol hydrochloride per packet

NUTRASWEET®
BRAND SWEETENER*

Phenylketonurics: contains phenylalanine
18.2 mg per 7.5 grams

60 packets
Rx only

PRINCIPAL DISPLAY PANEL - 450 gram Bottle Label

Pfizer
NDC 0009-0370-05

Flavored Colestid®
colestipol hydrochloride
for oral suspension

7.5 grams powder containing 5 grams
of colestipol hydrochloride per scoop

NUTRASWEET®
BRAND SWEETENER*

Phenylketonurics: contains
phenylalanine 18.2 mg per 7.5 grams

450 grams (60 scoops of 7.5 grams each)

Rx only

PRINCIPAL DISPLAY PANEL - 450 gram Bottle Carton

Pfizer
NDC 0009-0370-05

Flavored Colestid®
colestipol hydrochloride
for oral suspension

7.5 grams powder containing
5 grams of colestipol hydrochloride
per scoop

NUTRASWEET®
BRAND SWEETENER*

Phenylketonurics: contains
phenylalanine 18.2 mg per 7.5 grams

450 grams (60 scoops of 7.5 grams each)

Rx only